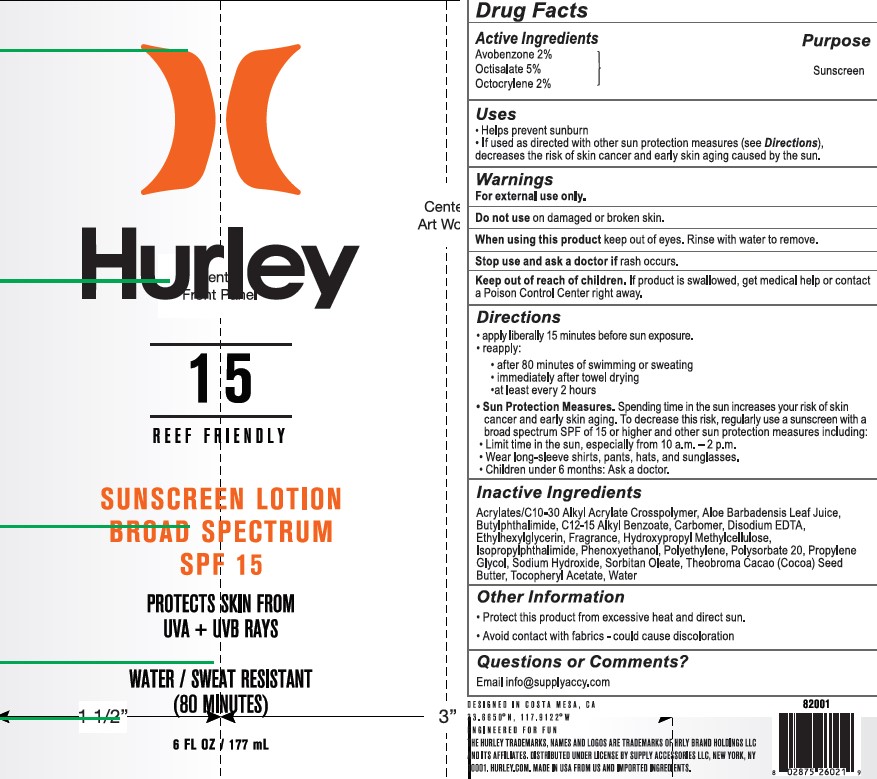 DRUG LABEL: Hurley
NDC: 58443-0432 | Form: LOTION
Manufacturer: Prime Enterprises Inc.
Category: otc | Type: HUMAN OTC DRUG LABEL
Date: 20210916

ACTIVE INGREDIENTS: OCTISALATE 48.25 mg/1 mL; AVOBENZONE 19.3 mg/1 mL; OCTOCRYLENE 19.3 mg/1 mL
INACTIVE INGREDIENTS: ISOPROPYLPHTHALIMIDE; HIGH DENSITY POLYETHYLENE; POLYSORBATE 20; CARBOMER COPOLYMER TYPE A; N-BUTYLPHTHALIMIDE; ETHYLHEXYLGLYCERIN; HYPROMELLOSES; SODIUM HYDROXIDE; ALOE VERA LEAF; ALKYL (C12-15) BENZOATE; ALPHA-TOCOPHEROL ACETATE; PHENOXYETHANOL; WATER; EDETATE DISODIUM ANHYDROUS; PROPYLENE GLYCOL; SORBITAN MONOOLEATE; COCOA BUTTER; CARBOMER HOMOPOLYMER, UNSPECIFIED TYPE

Hurley Sunscreen Lotion Broad Spectrum SPF 15

Active Ingredients

Avobenzone 2%, Octisalate 5%, Octocrylene 2%

Purpose

Sunscreen

Uses

Helps prevent sunburn

If used as directed with other sun protection measures (see Directions), decreases the risk of skin cancer and early skin aging caused by the sun.

Warnings

For external use only.

Do not use on damaged or broken skin.

When using this product keep out of eyes. Rinse with water to remove.

Stop use and ask a doctor if rash occurs.

Keep out of reach of children.

Keep put of reach of children. If product is swallowed, get medical help or contact a Poison Control Center right away.

Directions

- apply liberally 15 minutes before sun exposure.
- reapply:
- after 80 minutes of swimming or sweating
- immediately after towel drying
- at least every 2 hours
- Sun Protection Measures: Spending time in the sun increases your risk of skin cancer and early skin aging. To decrease this risk, regularly use a sunscreen with a Broad Spectrum SPF of 15 or higher and other sun protection measures including:
- Limit time in the sun, especially from 10 a.m. - 2 p.m.
- Wear long-sleeve shirts, pants, hats, and sunglasses.
- Children under 6 months: Ask a doctor.

Inactive Ingredients

Acrylates/C10-30 Alkyl Acrylate Crosspolymer, Aloe Barbadensis Leaf Juice, Butylphthalimide, C12-15 Alkyl Benzoate, Carbomer, Disodium EDTA, Ethylhexylglycerin, Fragrance, Hydroxypropyl Methylcellulose, Isopropylphthalimide, Phenoxyethanol, Polyethylene, Polysorbate 20, Propylene Glycol, Sodium Hydroxide, Sorbitan Oleate, Theobroma Cacao (Cocoa) Seed Butter, Tocopheryl Acetate, Water

Other Information

- Protect this product from excessive heat and direct sun.
- Avoid contact with fabrics - could cause discoloration

Questions or comments?

Email info@supplyaccy.com